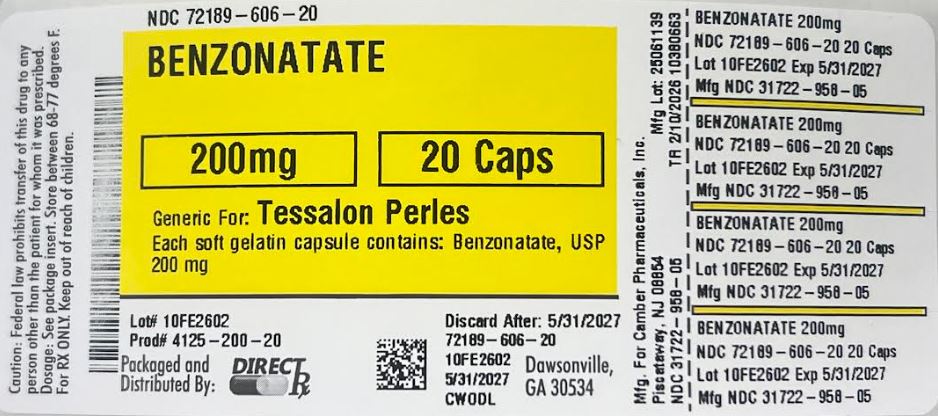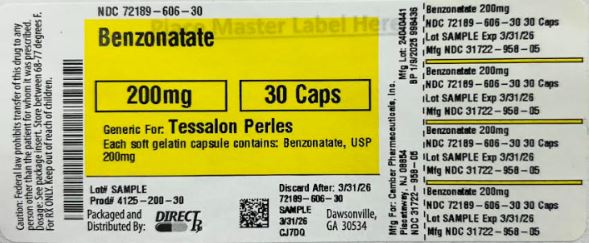 DRUG LABEL: Benzonatate
NDC: 72189-606 | Form: CAPSULE
Manufacturer: Direct_rx
Category: prescription | Type: HUMAN PRESCRIPTION DRUG LABEL
Date: 20260224

ACTIVE INGREDIENTS: BENZONATATE 200 mg/1 1
INACTIVE INGREDIENTS: WATER; MEDIUM-CHAIN TRIGLYCERIDES; ISOPROPYL ALCOHOL; FERROSOFERRIC OXIDE; GELATIN; NITROGEN; LECITHIN, SOYBEAN; D&C YELLOW NO. 10; PROPYLENE GLYCOL; HYPROMELLOSES; GLYCERIN

Benzonatate

DESCRIPTION

Benzonatate, a non-narcotic oral antitussive agent, is 2, 5, 8, 11, 14, 17, 20, 23, 26-nonaoxaoctacosan-28-yl p-(butylamino) benzoate; with a molecular weight of 603.7.

[benzonatate-struct]

Each benzonatate capsule USP contains:

Benzonatate, USP 100 mg

Each benzonatate capsule USP contains:

Benzonatate, USP 150 mg

Each benzonatate capsule USP contains:

Benzonatate, USP 200 mg

Benzonatate capsules USP also contain: bloom gelatin, glycerin, purified water, medium chain triglycerides, lecithin, isopropyl alcohol, nitrogen.

100 mg and 200 mg capsules also contain D&C Yellow No. 10.

150 mg capsules also contain FD&C Yellow No. 6 powder.

Each capsule also contains black iron oxide, propylene glycol, hypromellose as imprinting ink.

CLINICAL PHARMACOLOGY

Benzonatate capsules acts peripherally by anesthetizing the stretch receptors located in the respiratory passages, lungs, and pleura by dampening their activity and thereby reducing the cough reflex at its source. It begins to act within 15 to 20 minutes and its effect lasts for 3 to 8 hours. Benzonatate capsules has no inhibitory effect on the respiratory center in recommended dosage.

INDICATIONS AND USAGE

Benzonatate capsules is indicated for the symptomatic relief of cough.

CONTRAINDICATIONS

Hypersensitivity to benzonatate or related compounds.

WARNINGS

Hypersensitivity

Severe hypersensitivity reactions (including bronchospasm, laryngospasm and cardiovascular collapse) have been reported which are possibly related to local anesthesia from sucking or chewing the capsule instead of swallowing it. Severe reactions have required intervention with vasopressor agents and supportive measures.

Psychiatric Effects

Isolated instances of bizarre behavior, including mental confusion and visual hallucinations, have also been reported in patients taking benzonatate capsules in combination with other prescribed drugs.

Accidental Ingestion and Death in Children

Keep benzonatate capsules out of reach of children. Accidental ingestion of benzonatate capsules resulting in death has been reported in children below age 10. Signs and symptoms of overdose have been reported within 15-20 minutes and death has been reported within one hour of ingestion. If accidental ingestion occurs, seek medical attention immediately (see OVERDOSAGE).

PRECAUTIONS

Benzonatate is chemically related to anesthetic agents of the para-amino-benzoic acid class (e.g. procaine; tetracaine) and has been associated with adverse CNS effects possibly related to a prior sensitivity to related agents or interaction with concomitant medication.

Information for patients

Swallow benzonatate capsules whole. Do not break, chew, dissolve, cut, or crush benzonatate capsules. Release of benzonatate from the capsule in the mouth can produce a temporary local anesthesia of the oral mucosa and choking could occur. If numbness or tingling of the tongue, mouth, throat, or face occurs, refrain from oral ingestion of food or liquids until the numbness has resolved. If the symptoms worsen or persist, seek medical attention.

Keep benzonatate capsules out of reach of children. Accidental ingestion resulting in death has been reported in children. Signs and symptoms of overdose have been reported within 15-20 minutes and death has been reported within one hour of ingestion. Signs and symptoms may include restlessness, tremors, convulsions, coma and cardiac arrest. If accidental ingestion occurs, seek medical attention immediately.

Overdosage resulting in death may occur in adults.

Do not exceed a single dose of 200 mg and a total daily dosage of 600 mg. If you miss a dose of benzonatate capsules, skip that dose and take the next dose at the next scheduled time. Do not take 2 doses of benzonatate capsules at one time.

Usage in Pregnancy

Pregnancy Category C

Animal reproduction studies have not been conducted with benzonatate capsules. It is also not known whether benzonatate capsules can cause fetal harm when administered to a pregnant woman or can affect reproduction capacity. Benzonatate capsules should be given to a pregnant woman only if clearly needed.

Nursing mothers

It is not known whether this drug is excreted in human milk. Because many drugs are excreted in human milk caution should be exercised when benzonatate capsules is administered to a nursing woman.

Carcinogenesis, mutagenesis, impairment of fertility

Carcinogenicity, mutagenicity, and reproduction studies have not been conducted with benzonatate capsules.

Pediatric Use

Safety and effectiveness in children below the age of 10 have not been established. Accidental ingestion resulting in death has been reported in children below age 10. Keep out of reach of children.

Potential Adverse Reactions to benzonatate capsules may include:

Hypersensitivity reactions including bronchospasm, laryngospasm, cardiovascular collapse possibly related to local anesthesia from chewing or sucking the capsule.

CNS: sedation; headache; dizziness; mental confusion; visual hallucinations.

GI: constipation; nausea; GI upset.

Dermatologic: pruritus; skin eruptions.

Other: nasal congestion; sensation of burning in the eyes; vague “chilly” sensation; numbness of the chest; hypersensitivity.

Deliberate or accidental overdose has resulted in death, particularly in children.

OVERDOSAGE

Intentional and unintentional overdose may result in death, particularly in children.

The drug is chemically related to tetracaine and other topical anesthetics and shares various aspects of their pharmacology and toxicology. Drugs of this type are generally well absorbed after ingestion.

Signs and Symptoms

The signs and symptoms of overdose of benzonatate have been reported within 15-20 minutes. If capsules are chewed or dissolved in the mouth, oropharyngeal anesthesia will develop rapidly, which may cause choking and airway compromise.

CNS stimulation may cause restlessness and tremors which may proceed to clonic convulsions followed by profound CNS depression. Convulsions, coma, cerebral edema and cardiac arrest leading to death have been reported within 1 hour of ingestion.

Treatment:

In case of overdose, seek medical attention immediately. Evacuate gastric contents and administer copious amounts of activated charcoal slurry. Even in the conscious patient, cough and gag reflexes may be so depressed as to necessitate special attention to protection against aspiration of gastric contents and orally administered materials. Convulsions should be treated with a short-acting barbiturate given intravenously and carefully titrated for the smallest effective dosage. Intensive support of respiration and cardiovascular-renal function is an essential feature of the treatment of severe intoxication from overdosage.

Do not use CNS stimulants.

DOSAGE AND ADMINISTRATION

Adults and Children over 10 years of age: Usual dose is one 100 mg, 150 mg or 200 mg capsule three times a day as needed for cough. If necessary to control cough, up to 600 mg daily in three divided doses may be given. Benzonatate capsules should be swallowed whole. Benzonatate capsules are not to be broken, chewed, dissolved, cut or crushed.

HOW SUPPLIED

Benzonatate Capsules, USP are available in 100 mg, 150 mg and 200 mg dosage strengths.

The 100 mg capsules are yellow round capsules containing clear to light yellow liquid, printed with ‘1’ sign in black ink.

NDC 31722-956-30 bottles of 30 capsules

NDC 31722-956-01 bottles of 100 capsules

NDC 31722-956-05 bottles of 500 capsules

The 150 mg capsules are orange round capsules containing clear, light yellow to orange liquid, printed with ‘2’ sign in black ink.

NDC 31722-957-30 bottles of 30 capsules

NDC 31722-957-01 bottles of 100 capsules

NDC 31722-957-05 bottles of 500 capsules

The 200 mg capsules are yellow round capsules containing clear to light yellow liquid, printed with ‘3’ sign in black ink.

NDC 72189-606-20 bottles of 20 capsules

NDC 72189-606-30 bottles of 30 capsules

NDC 72189-606-30 bottles of 100 capsules

NDC 72189-606-30 bottles of 500 capsules

STORAGE AND HANDLING

Store at 20°C to 25°C (68°F to77°F) [see USP Controlled Room Temperature].

Protect from light. Dispense in tight, light-resistant container as defined in the USP with a child-resistant closure.

Manufactured by:

Ascent Pharmaceuticals, Inc.

Central Islip, NY 11722

Manufactured for:

Camber Pharmaceuticals, Inc.

Piscataway, NJ 08854

Rev: 07/21